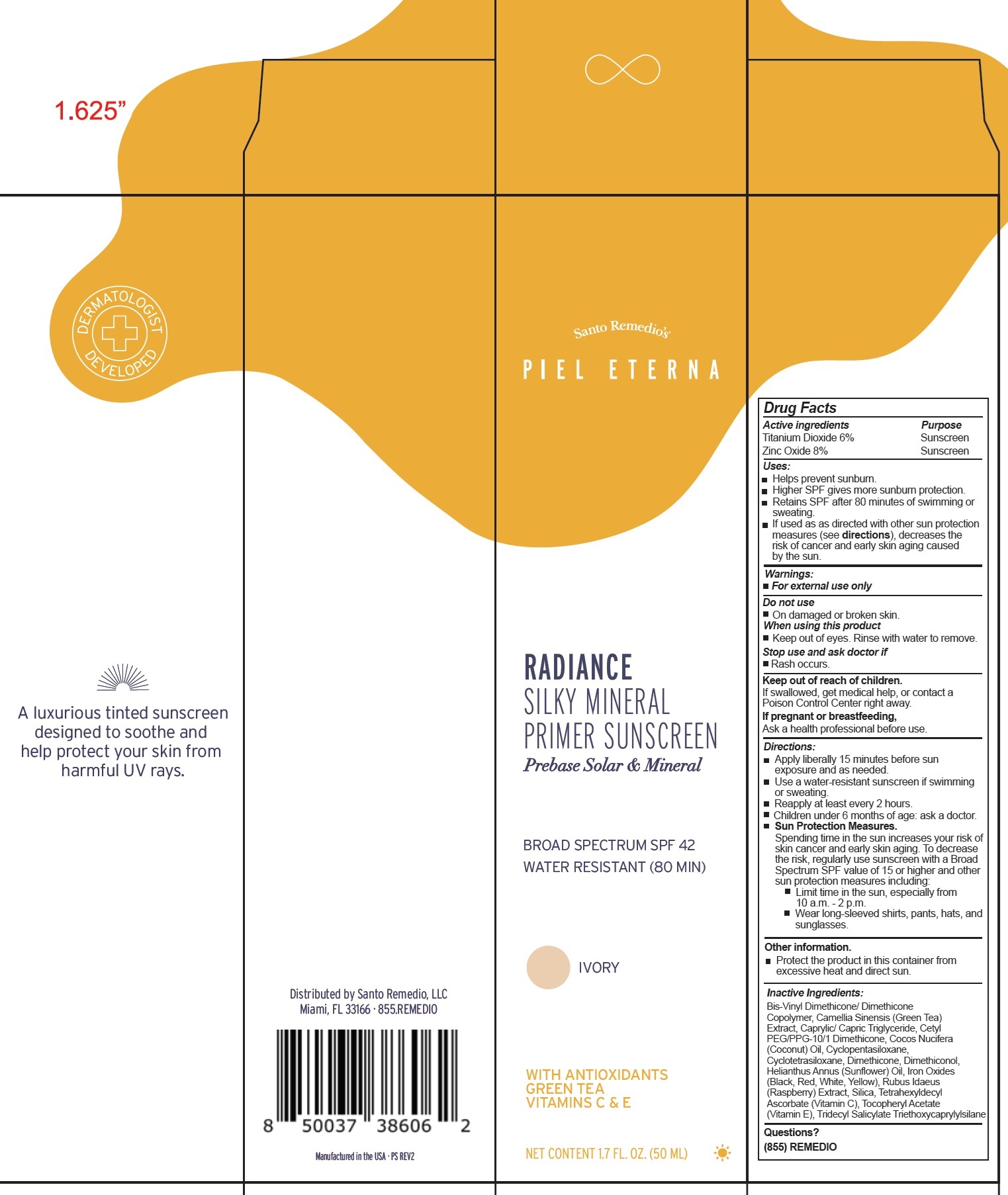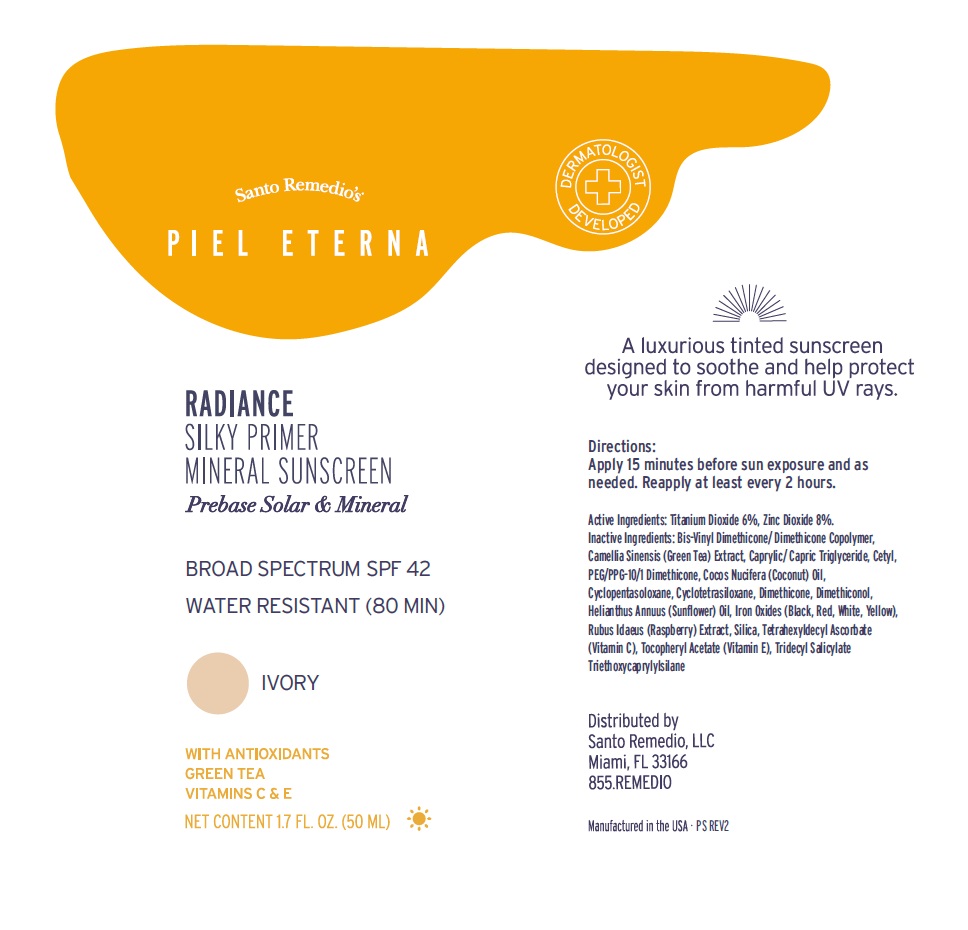 DRUG LABEL: SANTO REMEDIOS RADIANCE SILKY MINERAL PRIMER SUNSCREEN SPF 42 IVORY
NDC: 81352-518 | Form: LIQUID
Manufacturer: SANTO REMEDIO LLC
Category: otc | Type: HUMAN OTC DRUG LABEL
Date: 20240805

ACTIVE INGREDIENTS: TITANIUM DIOXIDE 60 mg/1 mL; ZINC OXIDE 80 mg/1 mL
INACTIVE INGREDIENTS: GREEN TEA LEAF; MEDIUM-CHAIN TRIGLYCERIDES; COCONUT OIL; CYCLOMETHICONE 5; CYCLOMETHICONE 4; DIMETHICONE; HELIANTHUS ANNUUS FLOWERING TOP; FERRIC OXIDE RED; RASPBERRY; SILICON DIOXIDE; TETRAHEXYLDECYL ASCORBATE; .ALPHA.-TOCOPHEROL ACETATE

SANTO REMEDIOS RADIANCE SILKY MINERAL PRIMER SUNSCREEN SPF-42 IVORY

Active ingredients

Titanium Dioxide 6%
Zinc Oxide 8%

Purpose

Sunscreen

Uses:

- Helps prevent sunburn.
- Higher SPF gives more sunburn protection.
- Retains SPF after 80 minutes of swimming or sweating.
- If used as as directed with other sun protection measures (see directions), decreases the risk of cancer and early skin aging caused by the sun.

Warnings:

- For external use only

Do not use

- On damaged or broken skin.

When using this product

- Keep out of eyes. Rinse with water to remove.

Stop use and ask doctor if

- Rash occurs.

Keep out of reach of children.

If swallowed, get medical help, or contact a Poison Control Center right away.

If pregnant or breastfeeding,

Ask a health professional before use.

Directions:

- Apply liberally 15 minutes before sun exposure and as needed.
- Use a water-resistant sunscreen if swimming or sweating.
- Reapply at least every 2 hours.
- Children under 6 months of age: ask a doctor.
- Sun Protection Measures. Spending time in the sun increases your risk of skin cancer and early skin aging. To decrease the risk, regularly use sunscreen with a Broad Spectrum SPF value of 15 or higher and other sun protection measures including:
- Limit time in the sun, especially from 10 a.m. - 2 p.m.
- Wear long-sleeved shirts, pants, hats, and sunglasses.

Other information.

- Protect the product in this container from excessive heat and direct sun.

Inactive Ingredients:

Bis-Vinyl Dimethicone/ Dimethicone Copolymer, Camellia Sinensis (Green Tea) Extract, Caprylic/ Capric Triglyceride, Cetyl PEG/PPG-10/1 Dimethicone, Cocos Nucifera (Coconut) Oil, Cyclopentasiloxane, Cyclotetrasiloxane, Dimethicone, Dimethiconol, Helianthus Annus (Sunflower) Oil, Iron Oxides (Black, Red, White, Yellow), Rubus Idaeus (Raspberry) Extract, Silica, Tetrahexyldecyl Ascorbate (Vitamin C), Tocopheryl Acetate(Vitamin E), Tridecyl Salicylate Triethoxycaprylylsilane

Questions?

(855) REMEDIO